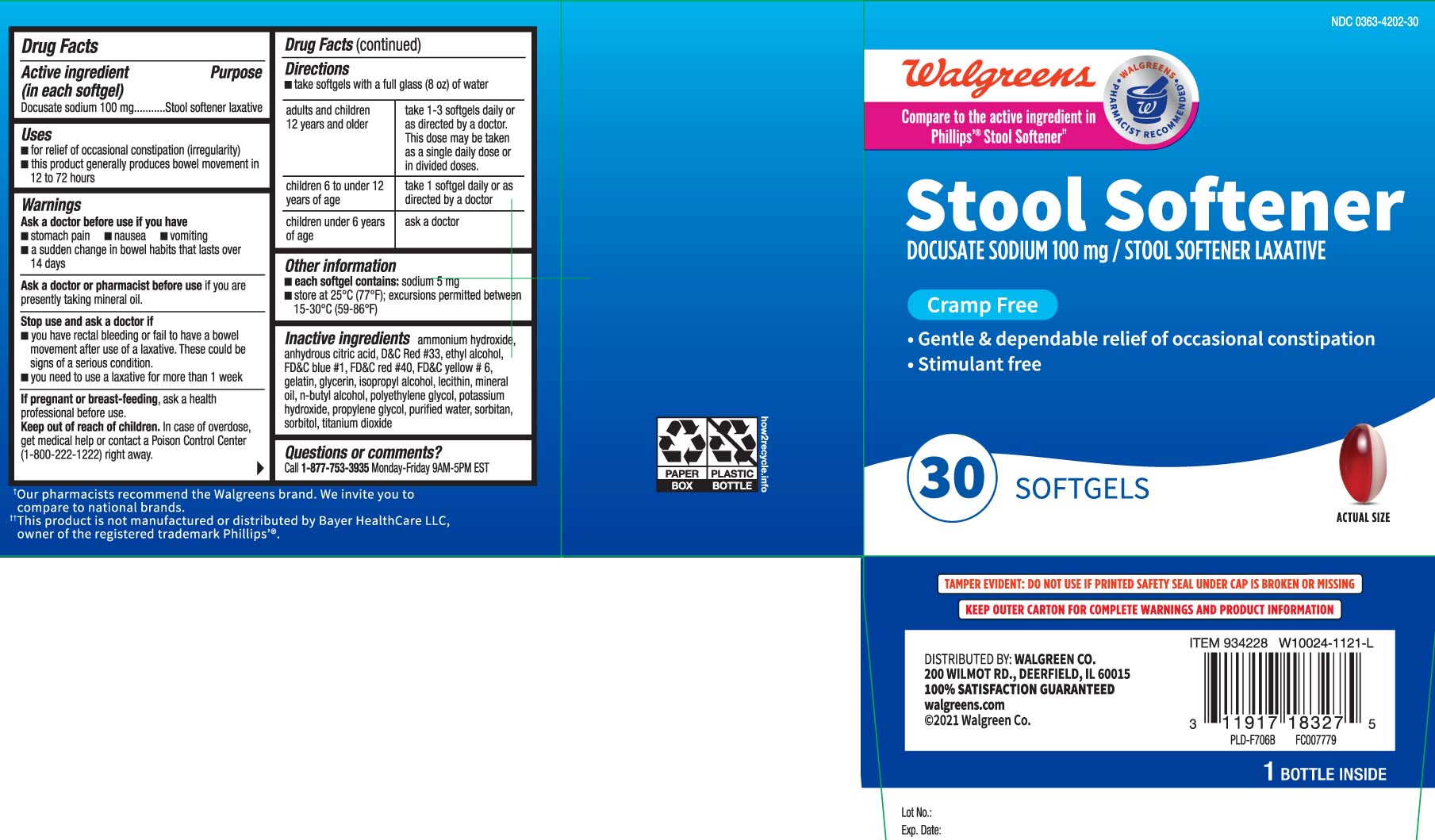 DRUG LABEL: Stool Softener Laxative
NDC: 0363-4202 | Form: CAPSULE, LIQUID FILLED
Manufacturer: Walgreens
Category: otc | Type: HUMAN OTC DRUG LABEL
Date: 20240710

ACTIVE INGREDIENTS: DOCUSATE SODIUM 100 mg/1 1
INACTIVE INGREDIENTS: D&C RED NO. 33; FD&C BLUE NO. 1; FD&C RED NO. 40; FD&C YELLOW NO. 6; GELATIN; GLYCERIN; POLYETHYLENE GLYCOL, UNSPECIFIED; PROPYLENE GLYCOL; WATER; SORBITAN; SORBITOL; TITANIUM DIOXIDE; AMMONIA; ANHYDROUS CITRIC ACID; ALCOHOL; ISOPROPYL ALCOHOL; LECITHIN, SOYBEAN; MINERAL OIL; BUTYL ALCOHOL; POTASSIUM HYDROXIDE

Drug Facts

Active ingredient (in each softgel)

Docusate sodium 100 mg

Purpose

Stool softener laxative

Uses

- for relief of occasional constipation (irregularity)
- this product generally produces bowel movement in 12 to 72 hours

Warnings

Ask a doctor before use if you have

- stomach pain
- nausea
- vomiting
- a sudden change in bowel habits that lasts over 14 days

Ask a doctor or pharmacist before use

if you are presently taking mineral oil

Stop use and ask a doctor if

- you have rectal bleeding or fail to have a bowel movement after use of a laxative. These could be signs of a serious condition.
- you need to use a laxative for more than 1 week

If pregnant or breast-feeding,

ask a health professional before use.

Keep out of reach of children.

In case of overdose, get medical help or contact a Poison Control Center (1-800-222-1222) right away.

Directions

- take softgels with a full glass (8 oz) of water

adults and children 12 years and older | take 1-3 softgels daily or as directed by a doctor.; This dose may be taken as a single daily dose or in divided doses.
children 6 to under 12 years of age | take 1 softgel daily or as directed by a doctor
children under 6 years of age | ask a doctor

Other information

- each softgel contains: sodium 5 mg
- store at 25ºC (77ºF); excursions permitted between 15-30ºC (59-86ºF)

Inactive ingredients

ammonium hydroxide, anhydrous citric acid, D&C red #33*, ethyl alcohol, FD&C blue #1, FD&C red #40, FD&C yellow #6, gelatin, glycerin, isopropyl alcohol, lecithin, mineral oil, n-butyl alcohol, polyethylene glycol, potassium hydroxide, propylene glycol, purified water, sorbitan, sorbitol, titanium dioxide

Questions or comments?

Call 1-877-753-3935 Monday-Friday 9AM-5PM EST

Principal Display Panel

Compare to the active ingredient in Phillips® Stool Softener††

Stool Softener

DOCUSATE SODIUM 100 mg / STOOL SOFTENER LAXATIVE

Cramp Free

- Gentle & dependable relief of occasional constipation
- Stimulant free

SOFTGELS

††This product is not manufactured or distributed by Bayer HealthCare LLC., owner of the registered trademark Phillips'®

TAMPER EVIDENT: DO NOT USE IF PRINTED SAFETY SEAL UNDER CAP IS BROKEN OR MISSING

KEEP OUTER CARTON FOR COMPLETE WARNINGS AND PRODUCT INFORMATION

DISTRIBUTED BY: WALGREEN CO.

200 WILMOT RD., DEERFIELD, IL 60015

walgreens.com

Product Label

WALGREENS Stool Softener Laxative